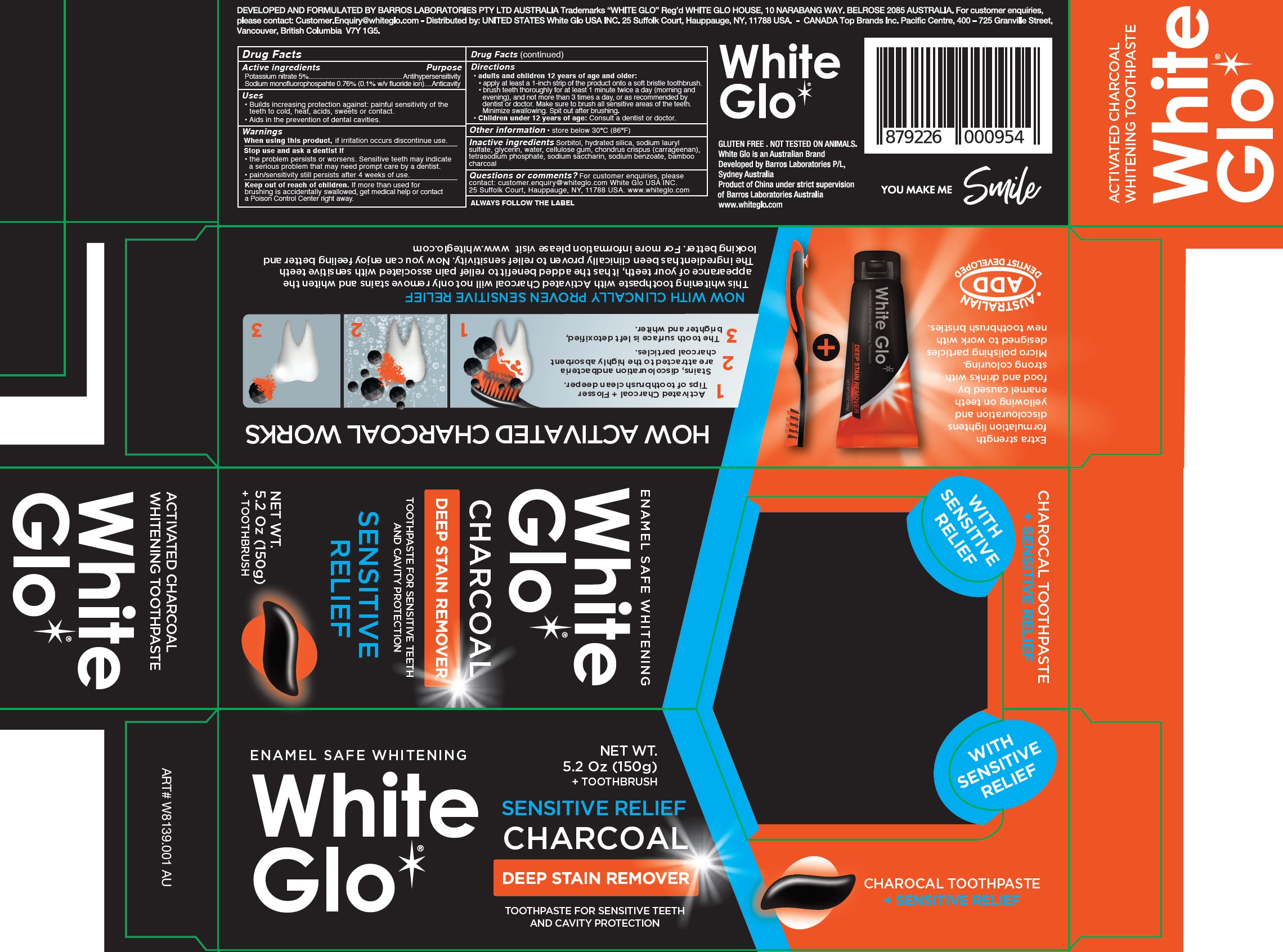 DRUG LABEL: WHITE GLO CHARCOAL SENSITIVE
NDC: 73656-011 | Form: KIT | Route: DENTAL
Manufacturer: WHITE GLO USA INC
Category: otc | Type: HUMAN OTC DRUG LABEL
Date: 20250226

ACTIVE INGREDIENTS: POTASSIUM NITRATE 50 mg/1 g; SODIUM MONOFLUOROPHOSPHATE 50 mg/1 g
INACTIVE INGREDIENTS: SORBITOL; HYDRATED SILICA; SODIUM LAURYL SULFATE; GLYCERIN; WATER; CARBOXYMETHYLCELLULOSE SODIUM, UNSPECIFIED FORM; CHONDRUS CRISPUS CARRAGEENAN; SACCHARIN SODIUM; SODIUM BENZOATE; ACTIVATED CHARCOAL

WHITE GLO CHARCOAL SENSITIVE TOOTHPASTE Kit

Active ingredients

Potassium nitrate 5%

Sodium monofluorophospahte 0.76% (0.1% w/v fluoride ion)

Purpose

Antihypersensitivity

Anticavity

Uses

• Builds increasing protection against: painful sensitivity of the teeth to cold, heat, acids, sweets or contact. • Aids in the prevention of dental cavities.

Warnings

When using this product,

if irritation occurs discontinue use.

Stop use and ask a dentist if

• the problem persists or worsens. Sensitive teeth may indicate a serious problem that may need prompt care by a dentist. • pain/sensitivity still persists after 4 weeks of use.

Keep out of reach of children.

If more than used for brushing is accidentally swallowed, get medical help or contact a Poison Control Center right away.

Directions

• adults and children 12 years of age and older: • apply at least a 1-inch strip of the product onto a soft bristle toothbrush. • brush teeth thoroughly for at least 1 minute twice a day (morning and evening), and not more than 3 times a day, or as recommended by dentist or doctor. Make sure to brush all sensitive areas of the teeth. Minimize swallowing. Spit out after brushing. • Children under 12 years of age: Consult a dentist or doctor.

Other information

• store below 30ºC (86ºF)

Inactive ingredients

Sorbitol, hydrated silica, sodium lauryl sulfate, glycerin, water, cellulose gum, chondrus crispus (carrageenan), tetrasodium phosphate, sodium saccharin, sodium benzoate, bamboo charcoal

Questions or comments?

For customer enquiries, please contact: customer.enquiry@whiteglo.com White Glo USA INC. 25 Suffolk Court, Hauppauge, NY, 11788 USA. www.whiteglo.com